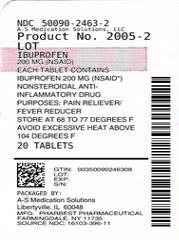 DRUG LABEL: Ibuprofen
NDC: 50090-2463 | Form: TABLET
Manufacturer: A-S Medication Solutions
Category: otc | Type: HUMAN OTC DRUG LABEL
Date: 20190425

ACTIVE INGREDIENTS: IBUPROFEN 200 mg/1 1
INACTIVE INGREDIENTS: SILICON DIOXIDE; CROSCARMELLOSE SODIUM; MAGNESIUM STEARATE; MICROCRYSTALLINE CELLULOSE; POLYETHYLENE GLYCOL 3350; POLYVINYL ALCOHOL, UNSPECIFIED; STARCH, CORN; FERRIC OXIDE RED; TALC; TITANIUM DIOXIDE

Drug Facts

Active ingredient (in each tablet)

Ibuprofen 200 mg (NSAID)*

*nonsteroidal anti- inflammatory drug

Purpose

Pain Reliever/ Fever Reducer

Uses

temporarily relieves minor aches and pain due to:

- headache
- toothache
- backache
- menstrual cramps
- the common cold
- muscular aches
- minor pain of arthritis
- temporarily reduces fever

Warnings

Allergy alert:

Ibuprofen may cause a severe allergic reaction, especially in people allergic to Aspirin. Symptoms may include

- hives
- facial swelling
- asthma (wheezing)
- shock
- skin reddening
- rash
- blisters

If an allergic reaction occurs, stop use and seek medical help right away.

Stomach bleeding warning:

This product contains an NSAID, which may cause severe stomach bleeding. The chance is higher if you

- are age 60 or older
- have had stomach ulcers or bleeding problems
- take a blood thinning (anticoagulant) or steroid drug
- take other drugs containing prescription or non prescription NSAIDs (aspirin, ibuprofen, naproxen, or others)
- have 3 or more alcoholic drinks everyday while using this product
- take more or for a longer time than directed

Do not use

- if you have ever had an allergic reaction to any other pain reliever/ fever reducer
- right before or after heart surgery

Ask a doctor before use if

- stomach bleeding warning applies to you
- you have problems or serious side effects from taking pain relievers or fever reducers
- you have a history of stomach problems, such as heartburn
- you have high blood pressure, heart disease, liver cirrhosis, kidney disease or asthma
- you are taking a diuretic

Ask a doctor or pharmacist before use if you are

- under a doctor's care for any serious condition
- taking aspirin for heart attack or stroke, because ibuprofen may decrease this benefit of aspirin
- taking any other drug

when using this product

- take with food or milk if stomach upset occurs
- the risk of heart attack or stroke may increase if you use more than directed or for longer than directed

Stop use and ask a doctor if

- you experience any of the following signs of stomach bleeding:
- feel faint
- vomit blood
- have bloody or black stools
- have stomach pain that does not get better
- pain gets worse or last for more than 10 days
- fever gets worse or last more than 3 days
- redness or swelling is present in the painful area
- any new symptoms appear

If pregnant or breast feeding,

ask a health professional before use. It is especially important not to use ibuprofen during the last 3 months of pregnancy unless definitely directed to do so by a doctor because it may cause problems in the unborn child or complications during delivery.

Keep out of reach of children.

In case of overdose, get medical help or contact a Poison Control Center right away (1-800-222-1222). This Package for Households Without Young Children.

Directions

- do not take more than directed

- the smallest effective dose should be used

adults and children 12 years and older | - take 1 tablet every4 to 6 hours while symptoms persist - if pain or fever does not respond to 1 tablet, 2 tablets may be used - do not exceed 6 tablets in 24 hours, unless directed by a doctor
children under 12 years | - consult a doctor

Other information

- Tamper Evident: do not use if safety seal under cap is broken or missing
- store at room temperature (20o- 25oC)
- avoid excessive heat above 40oC (104oF)

Inactive Ingredients:

colloidal silicon dioxide, croscarmellose sodium, magnesium stearate, microcrystalline cellulose, polyethylene glycol, polyvinyl alcohol, pregelatinized starch, red iron oxide, talc & titanium dioxide

Questions? Adverse drug event call: (866)562-2756 Mon-Fri: 8 AM to 4 PM

*This product is not manufactured or distributed by Pfizer Consumer Products, owner of the registered trademark ADVIL®.

Manufactured for:

Pharbest Pharmaceuticals, Inc.,

Farmingdale, NY 11735

LRev 02/16

HOW SUPPLIED

Product: 50090-2463

NDC: 50090-2463-2 20 TABLET in a BOTTLE

NDC: 50090-2463-3 24 TABLET in a BOTTLE

NDC: 50090-2463-4 40 TABLET in a BOTTLE

NDC: 50090-2463-5 30 TABLET in a BOTTLE

NDC: 50090-2463-6 28 TABLET in a BOTTLE

NDC: 50090-2463-7 60 TABLET in a BOTTLE

NDC: 50090-2463-8 100 TABLET in a BOTTLE

NDC: 50090-2463-0 50 TABLET in a BOTTLE